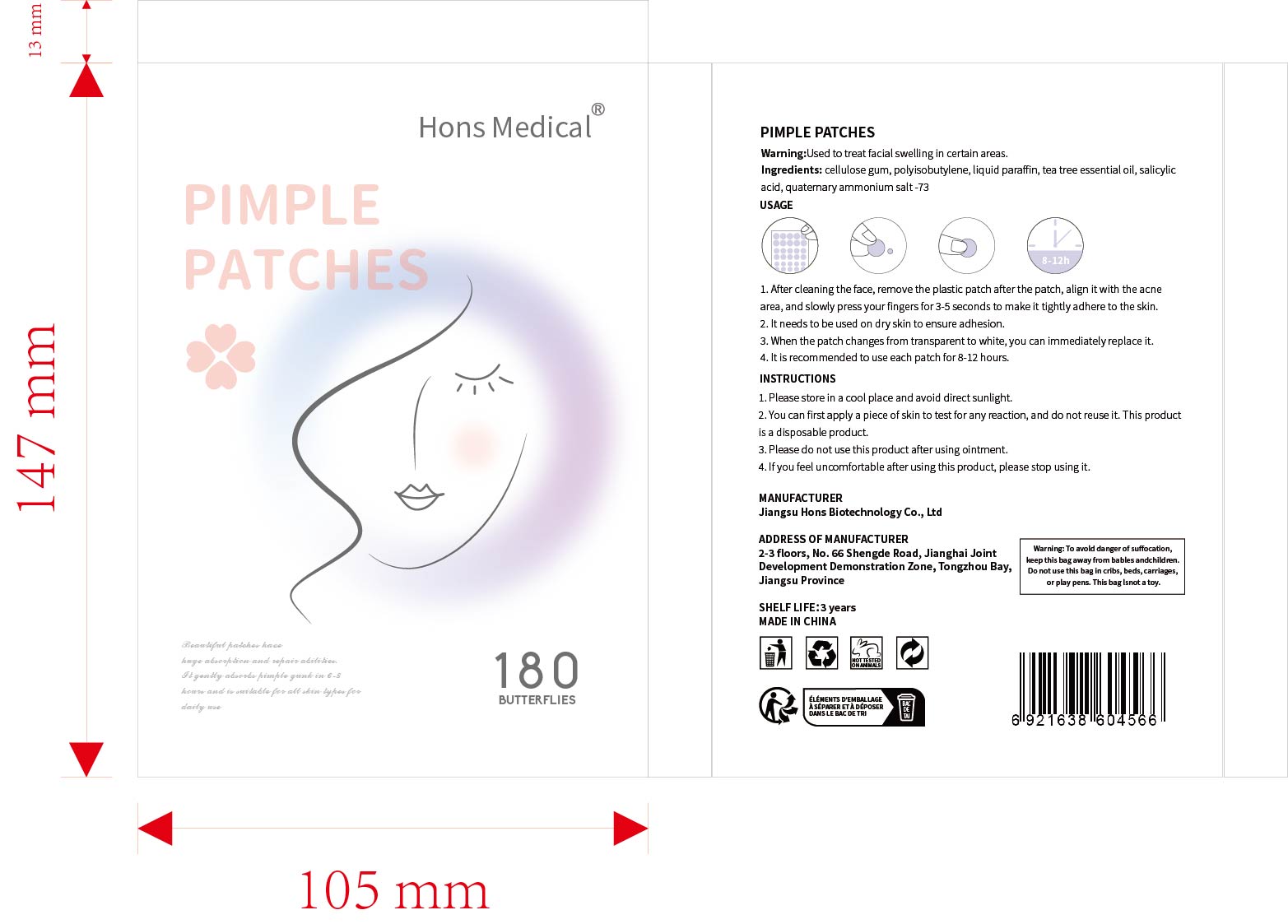 DRUG LABEL: SYAnti-acnePatch
NDC: 84778-026 | Form: GEL
Manufacturer: Guangzhou Yixin Cross-border E-commerce Co., Ltd.
Category: otc | Type: HUMAN OTC DRUG LABEL
Date: 20241105

ACTIVE INGREDIENTS: SALICYLIC ACID 0.5 g/0.5 g
INACTIVE INGREDIENTS: POLYISOBUTYLENE (55000 MW); PARAFFINUM LIQUIDUM; TEA TREE OIL; CELLULOSE GUM

COMPONENTS

salicylic acid 0.5g

PURPOSE

For the treatment of acne and pimples on the face

INDICATIONS AND USAGE

Clean your skin first, choose a suitable size and stick it on the acne, wait for a few hours, and then wash it with warm water

WARNINGS

For external use only.

If sensitive irritation occurs, please stop using and store in a cool and dry place.

DOSAGE AND ADMINISTRATION

For external use only.

DO NOT USE

Please make sure your skin is clean before use. Avoid using on open wounds or skin with allergic reactions.

WHEN USING

Clean the skin with warm water to ensure that the skin surface is clean. Choose the appropriate size of acne patch that can completely cover the acne. Let the acne patch stay on the skin for a sufficient time. After the use time is over, you can clean the skin with warm water.

Do not use on open wounds or allergic skin.

KEEP OUT OF REACH OF CHILDREN

If sxralowed, get medical help or contact a Poison Conirol Cenler ngiht away.

INACTIVE INGREDIENT

cellulose gum, polyisobutylene, liquid paraffin, tea tree essential oil, quaternary ammonium salt-73